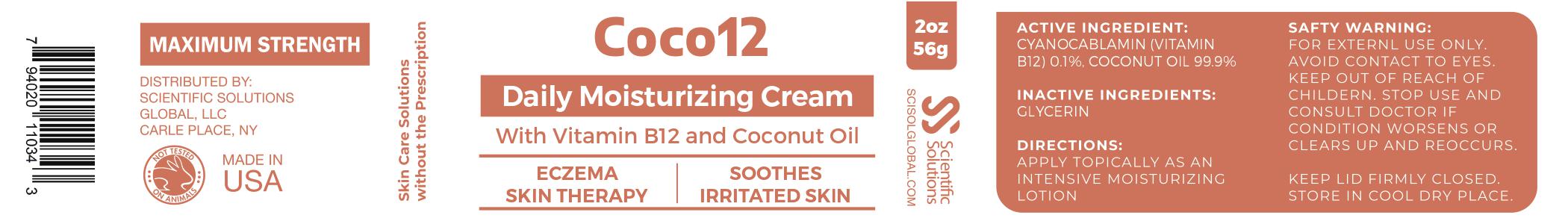 DRUG LABEL: Coco12
NDC: 81376-303 | Form: LOTION
Manufacturer: SSG Ventures Inc
Category: otc | Type: HUMAN OTC DRUG LABEL
Date: 20210111

ACTIVE INGREDIENTS: CYANOCOBALAMIN 0.05 g/0.05 g
INACTIVE INGREDIENTS: COCONUT OIL

Coco 12

PACKAGE LABEL

Active Ingredient

CYANOCABLAMIN (VITAMIN B12) 0.1%, COCONUT OIL 99.9%

Inactive Ingredients:

Glycerin

Directions:

APPLY TOPICALLY AS AN INTENSIVE MOISTURIZING LOTION

SAFETY WARNING:

FOR EXTERNAL USE ONLY:

AVOID CONTACT TO EYES.

KEEP OUT OF REACH OF CHILDREN.

STOP USE AND CONSULT DOCTOR IF CONDITION WORSENS OR CLEARS UP AN REOCCURS.

KEEP LID FIRMLY CLOSED.

STORE IN COOL DRY PLACE

PURPOSE

ECZEMA SKIN THERAPY

SOOTHES IRRITATED SKIN

KEEP OUT OF REACH OF CHILDREN

INDICATIONS AND USAGE

ECZEMA SKIN THERAPY

SOOTHES IRRITATED SKIN